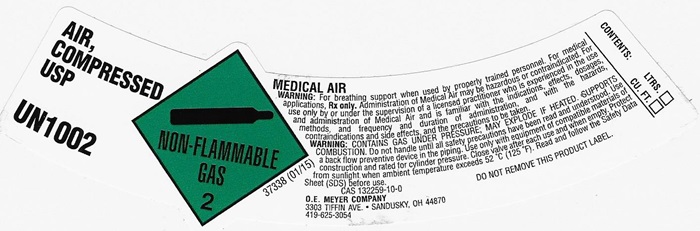 DRUG LABEL: AIR COMPRESSED
NDC: 47632-0025 | Form: GAS
Manufacturer: O.E. Meyer Company
Category: prescription | Type: HUMAN PRESCRIPTION DRUG LABEL
Date: 20241028

ACTIVE INGREDIENTS: OXYGEN 20 L/100 L
INACTIVE INGREDIENTS: NITROGEN

Air-Compressed

AIR, COMPRESSED LABEL

AIR, COMPRESSED USP UN1002 NON-FLAMMABLE GAS 2 37338 (01/15)

MEDICAL AIR

WARNING: For breathing support when used by properly trained personnel. For medical applications. Rx only. Administration of Medical Air may be hazardous or contraindicated. For use only by or under the supervision of a licensed practitioner who is experienced in the use and administration of Medical Air and is familiar with the indications, effects, dosages, methods, and frequency and duration of administration, and with the hazards, contraindications and side effects and the precautions to be taken.

WARNING: CONTAINS GAS UNDER PRESSURE; MAY EXPLODE IF HEATED, SUPPORTS COMBUSION. Do not handle until all safety precautions have been read and understood. Use a backflow preventive device I the piping. Use only with equipment of compatible materials of construction and rated for cylinder pressure. Close valve after each use and when empty. Protect from sunlight when ambient temperature exceeds 52°C (125°F). Read and follow the Safety Data Sheet (SDS) before use.

CAS 132259-10-0 DO NOT REMOVE THIS PRODUCT LABEL.

CONTENTS: LTRS. _______

CU. FT. _______

O.E. MEYER COMPANY

3303 TIFFIN AVE. • SANDUSKY, OH 44870

419-6253054